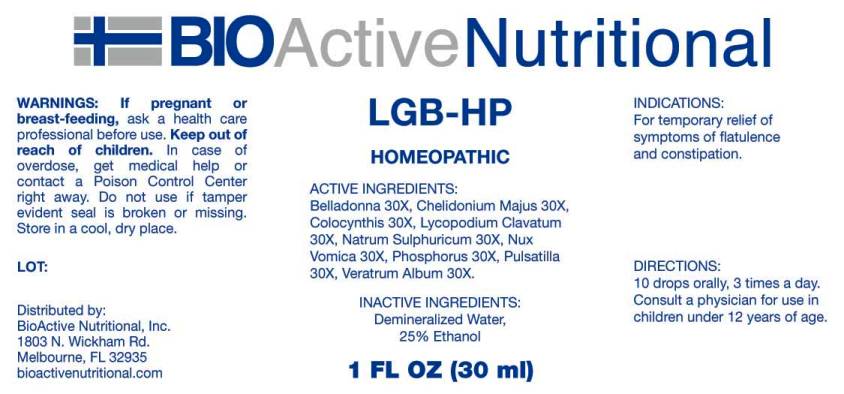 DRUG LABEL: LGB
NDC: 43857-0045 | Form: LIQUID
Manufacturer: BioActive Nutritional, Inc.
Category: homeopathic | Type: HUMAN OTC DRUG LABEL
Date: 20170118

ACTIVE INGREDIENTS: ATROPA BELLADONNA WHOLE 30 [hp_X]/1 mL; CHELIDONIUM MAJUS 30 [hp_X]/1 mL; CITRULLUS COLOCYNTHIS FRUIT PULP 30 [hp_X]/1 mL; LYCOPODIUM CLAVATUM SPORE 30 [hp_X]/1 mL; SODIUM SULFATE 30 [hp_X]/1 mL; STRYCHNOS NUX-VOMICA SEED 30 [hp_X]/1 mL; PHOSPHORUS 30 [hp_X]/1 mL; PULSATILLA VULGARIS 30 [hp_X]/1 mL; VERATRUM ALBUM ROOT 30 [hp_X]/1 mL
INACTIVE INGREDIENTS: WATER; ALCOHOL

Drug Facts:

ACTIVE INGREDIENTS:

Belladonna 30X, Chelidonium Majus 30X, Colocynthis 30X, Lycopodium Clavatum 30X, Natrum Sulphuricum 30X, Nux Vomica 30X, Phosphorus 30X, Pulsatilla (Vulgaris) 30X, Veratrum Album 30X.

INDICATIONS:

For temporary relief of symptoms of flatulence and constipation.

WARNINGS:

If pregnant or breast-feeding, ask a health care professional before use.

Keep out of reach of children. In case of overdose, get medical help or contact a Poison Control Center right away.

Do not use if tamper evident seal is broken or missing.

Store in cool, dry place.

DIRECTIONS:

10 drops orally, 3 times a day. Consult a physician for use in children under 12 years of age.

INACTIVE INGREDIENTS:

Demineralized Water, 25% Ethanol.

Keep out of reach of children. In case of overdose, get medical help or contact a Poison Control Center right away.

INDICATIONS:

For temporary relief of symptoms of flatulence and constipation.

QUESTIONS:

Distributed by:
BioActive Nutritional, Inc.
1803 N. Wickham Rd.
Melbourne, FL 32935
bioactivenutritional.com

PACKAGE LABEL DISPLAY:

BIOActive Nutritional

LGB HP

HOMEOPATHIC

1 FL OZ (30 ml)